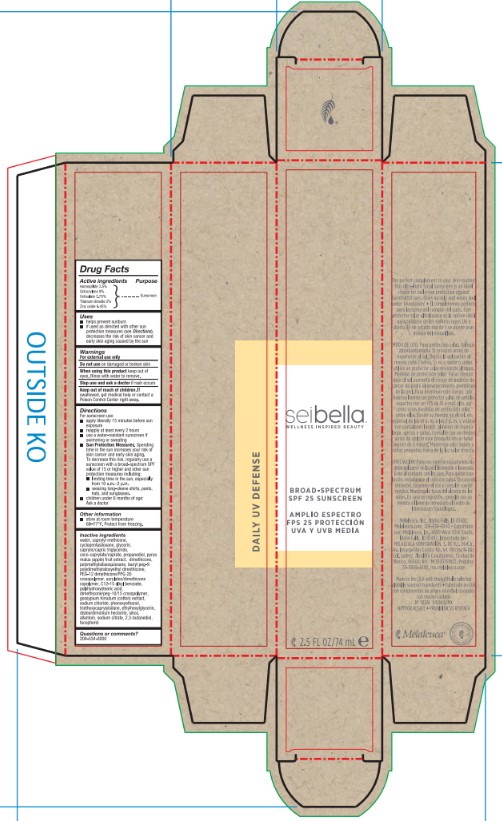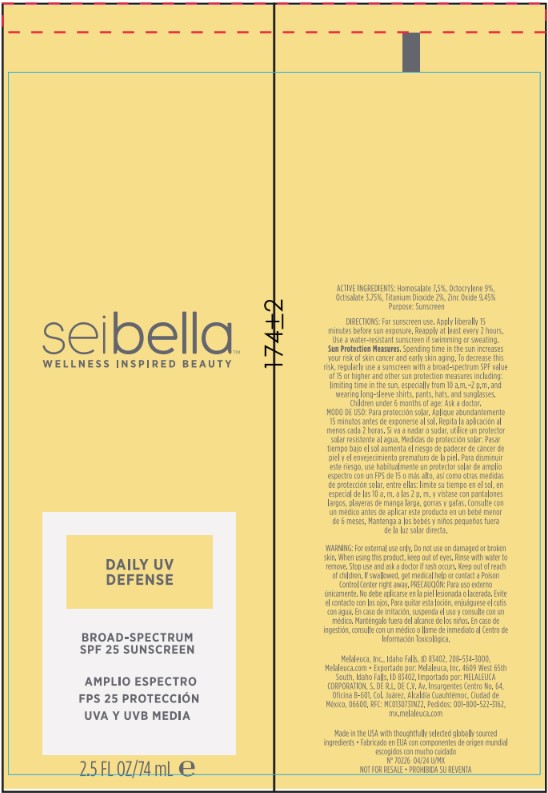 DRUG LABEL: Sei Bella Daily UV Defense
NDC: 54473-403 | Form: CREAM
Manufacturer: Melaleuca Inc.
Category: otc | Type: HUMAN OTC DRUG LABEL
Date: 20251231

ACTIVE INGREDIENTS: OCTOCRYLENE 0.225 g/74 mL; ZINC OXIDE 0.236 g/74 mL; HOMOSALATE 0.188 g/74 mL; OCTISALATE 0.094 g/74 mL; TITANIUM DIOXIDE 0.05 g/74 mL
INACTIVE INGREDIENTS: SILICON DIOXIDE; APPLE; POLYMETHYLSILSESQUIOXANE (4.5 MICRONS); PROPANEDIOL; GOSSYPIUM HIRSUTUM ROOT; SODIUM CITRATE; ALLANTOIN; WATER; CAPRYLYL TRISILOXANE; PHENOXYETHANOL; MEDIUM-CHAIN TRIGLYCERIDES; CYCLOMETHICONE 5; ALKYL (C12-15) BENZOATE; TOCOPHEROL; GLYCERIN; COCO-CAPRYLATE/CAPRATE; DIMETHICONE; 2-ETHYLHEXYL ACRYLATE, METHACRYLATE, METHYL METHACRYLATE, OR BUTYL METHACRYLATE/HYDROXYPROPYL DIMETHICONE COPOLYMER (30000-300000 MW); DIMETHICONE/PEG-10/15 CROSSPOLYMER; SODIUM CHLORIDE; TRIETHOXYCAPRYLYLSILANE; ETHYLHEXYLGLYCERIN; DISTEARDIMONIUM HECTORITE; 2,3-BUTANEDIOL; POLYHYDROXYSTEARIC ACID (2300 MW); LAURYL PEG-9 POLYDIMETHYLSILOXYETHYL DIMETHICONE; PEG-12 DIMETHICONE/PPG-20 CROSSPOLYMER

Sei Bella Daily UV Defense

Active Ingredients

Homosalate 7.5%
Octocrylene 9%
Octisalate 3.75%
Titanium Dioxide 2%
Zinc Oxide 9.45%

PURPOSE

sunscreen

INDICATIONS AND USAGE

helps prevent sunburn

if used as directed with other sun protection measures (see Directions), decreases the risk of skin cancer caused by the sun

Warnings

For external use only. Do not use on damaged or broken skin

When using this product keep out of eyes. Rinse with water to remove.

Stop use and ask a doctor if rash occurs

Keep out of reach of children. If swallowed, get medical help or contact a Poison Control Center right away.

DOSAGE AND ADMINISTRATION

Directions For sunscreen use:

- apply liberally 15 minutes before sun exposure
- reapply at least every 2 hours
- use a water-resistant sunscreen if swimming or sweating
- Sun Protection Measures. Spending time in the sun increases your risk of skin cancer and early skin aging. To decrease this risk, regularly use a sunscreen with a broad-spectrum SPF value of 15 or higher and other sun protection measures including:

limiting time in the sun, especially from 10 a.m. - 2 p.m.

wearing long-sleeve shirts, pants, hats, and sunglasses

- children under 6 months of age: Ask a doctor

STORAGE AND HANDLING

store at room temperature 68-77 F. Protect from freezing.

INACTIVE INGREDIENT

water, caprylyl methicone, cyclopentasiloxane, glycerin, caprylic/capric triglyceride, coco-caprylate/caprate, propanediol, pyrus malus (apple) fruit extract, dimethicone, polymethylsilsesquioxane, lauryl peg-9 polydimethylsiloxyethyl dimethicone, PEG-12 dimethicone/PPG-20 crosspolymer, acrylates/dimethicone copolymer, C12-15 alkyl benzoate, polyhydroxystearic acid, dimethicone/peg-10/15 crosspolymer, gossypium hirsutum (cotton) extract, sodium chloride, phenoxyethanol, triethoxycaprylylsilane, ethylhexylglycerin,disteardimonium hectorite, silica, allantoin, sodium citrate, 2,3-butanediol, tocopherol